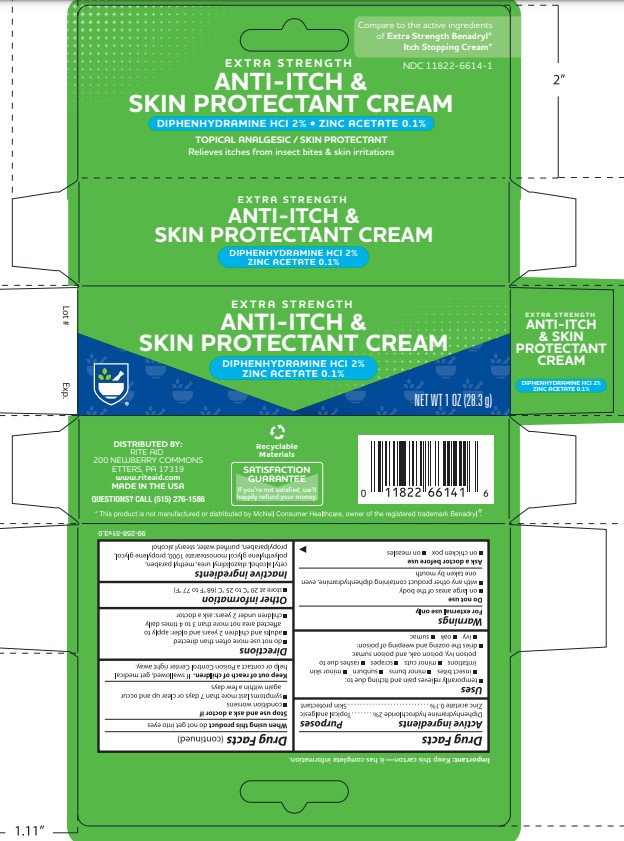 DRUG LABEL: Rite Aid Extra Strength Itch Stopping
NDC: 11822-6614 | Form: CREAM
Manufacturer: Rite Aid
Category: otc | Type: HUMAN OTC DRUG LABEL
Date: 20231211

ACTIVE INGREDIENTS: ZINC ACETATE 1 mg/1 g; DIPHENHYDRAMINE HYDROCHLORIDE 20 mg/1 g
INACTIVE INGREDIENTS: CETYL ALCOHOL; DIAZOLIDINYL UREA; GLYCERYL MONOSTEARATE; METHYLPARABEN; WATER; PROPYLPARABEN; PROPYLENE GLYCOL; PEG-40 STEARATE; PEG-100 STEARATE

Rite Aid Extra Strength Itch Stopping Cream

Active Ingredients

Diphenhydramine hydrochloride 2%

Zinc acetate 0.1%

Purpose

Diphenhydramine hydrochloride...............Topical anagesic

Zinc acetate..............................................Skin protectant

Uses

temporarliy relieves pain and itching due to:

- insect bites
- minor burns
- sunburn
- minor skin irritations
- minor cuts
- scrapes
- rashes due to poison ivy, poison oak, and poison sumac

dries the oozing and weeping due to poison:

- ivy
- oak
- sumac

Warnings

For external use only

Do not use

- on large areas of the body
- with any other product containing diphenhydramine, even one taken by mouth

Ask a doctor before use

- on chicken pox
- on measles

When using this product

do not get into eyes

Stop use and ask a doctor if

- condition worsens
- symptoms last more than 7 days or clear up and occur again within a few days

Keep out of reach of children

If swallowed, get medical help or contact a Poison Control Center right away

Directions

- do not use more often than directed
- adults and children 2 years and older: apply to affected area not more than 3 to 4 times daily
- children under 2 years: ask a doctor

Other Information

- store at 20º C to 25º C (68º F to 77º F)

Inactive Ingredients

cetyl alcohol, diazolidinyl urea, glyceryl stearate, methylparaben, PEG-40 stearate, PEG-100 stearate, propylene glycol, propylparaben, purified water

Package Label - 1oz (28g)

Extra Strength

Est. 1892 WEEKS&LEO Professional Health

ITCH STOPPING CREAM

Topical Analgesic / Skin Protectant

Net wt. 1 oz (28 g)